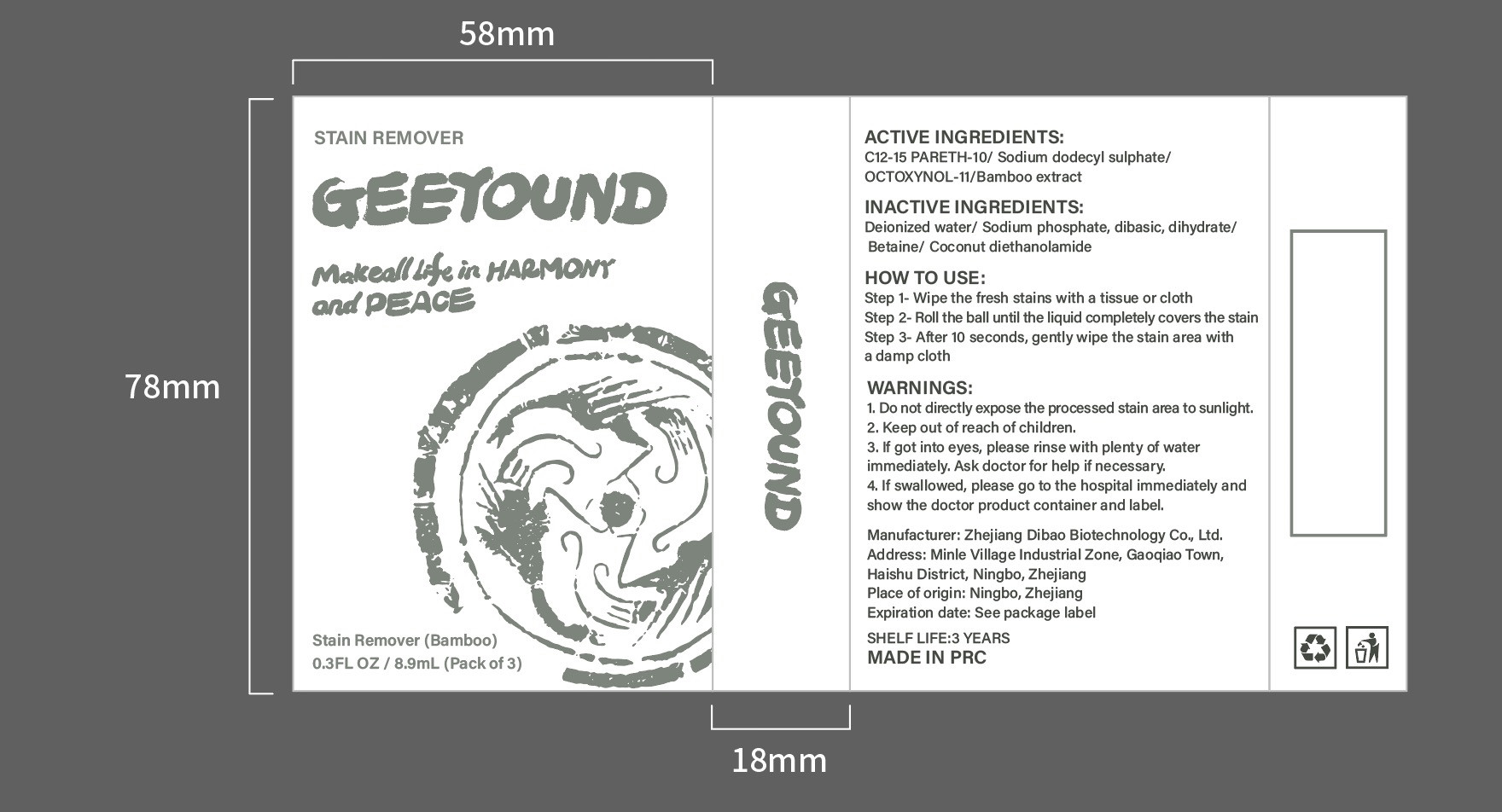 DRUG LABEL: Stain remover
NDC: 82371-003 | Form: LIQUID
Manufacturer: Zhejiang Dibao Biotechnology Co., Ltd.
Category: otc | Type: HUMAN OTC DRUG LABEL
Date: 20211228

ACTIVE INGREDIENTS: OCTOXYNOL-11 4 g/100 mL; BAMBUSA VULGARIS TOP 10.2 g/100 mL; SODIUM LAURYL SULFATE 8 g/100 mL; C12-15 PARETH-10 5 g/100 mL
INACTIVE INGREDIENTS: SODIUM PHOSPHATE, DIBASIC, DIHYDRATE; BETAINE; WATER; COCO DIETHANOLAMIDE

ACTIVE INGREDIENT

C12-15 PARETH-10 5%

Sodium dodecyl sulphate 8%

OCTOXYNOL-11 4%

Bamboo extract 10.2%

INACTIVE INGREDIENT

Deionized water

Sodium phosphate, dibasic, dihydrate

Betaine

Coconut diethanolamide

HOW TO USE

Step 1-Wipe the fresh stains with a tissue or cloth
Step 2- Roll the ball until the liquid completely covers the stain
Step 3- After 10 seconds, gently wipe the stain area witha damp cloth

INDICATIONS AND USAGE

Spray enough product where you need to clean up to cover the dirt.

Keep out of reach of children.

PURPOSE

In addition to stains

STORAGE AND HANDLING

Keep in a cool and dry place

WARNINGS

1.Do not directly expose the processed stain area to sunlight.
2.Keep out of reach of children.
3. If got into eyes, please rinse with plenty of water immediately. Ask doctor for help if necessary.
4. If swallowed, please go to the hospital immediately and show the doctor product container and label.